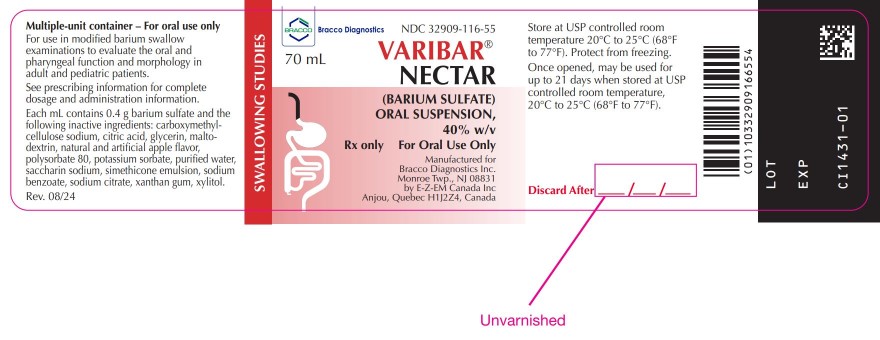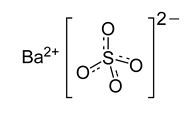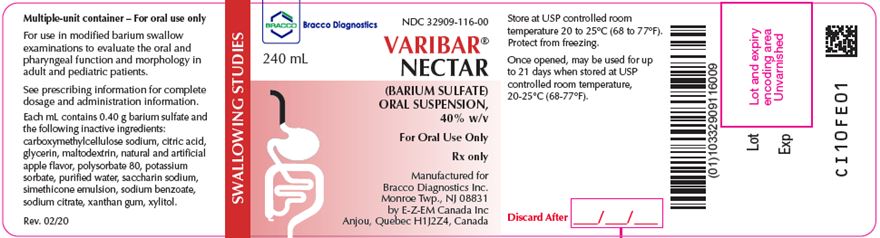 DRUG LABEL: Varibar Nectar
NDC: 32909-115 | Form: SUSPENSION
Manufacturer: E-Z-EM Canada Inc
Category: prescription | Type: HUMAN PRESCRIPTION DRUG LABEL
Date: 20241111

ACTIVE INGREDIENTS: Barium Sulfate 400 mg/1 mL
INACTIVE INGREDIENTS: anhydrous citric acid; carboxymethylcellulose sodium; dimethicone 350; dimethicone 1000; glycerin; maltodextrin; polysorbate 80; potassium sorbate; saccharin sodium; silicon dioxide; sodium benzoate; trisodium citrate dihydrate; water; xanthan gum; xylitol

HIGHLIGHTS OF PRESCRIBING INFORMATION

These highlights do not include all the information needed to use VARIBAR NECTAR safely and effectively. See full prescribing information for VARIBAR NECTAR.
VARIBAR NECTAR (barium sulfate) oral suspension
Initial U.S. Approval: 2016

1 INDICATIONS AND USAGE

VARIBAR NECTAR is a radiographic contrast agent indicated for use in modified barium swallow examinations to evaluate the oral and pharyngeal function and morphology in adult and pediatric patients. (1)

2 DOSAGE AND ADMINISTRATION

- For oral use only – administered by syringe, spoon, or cup. The recommended dose is:
- Adults: 5 mL
- Pediatric patients 6 months and older: 1-3 mL
- Pediatric patients younger than 6 months of age: 0.5-1 mL
- Maximum cumulative dose: 30 mL
- During a single modified barium swallow examination, multiple doses of VARIBAR NECTAR may be administered. (2)

3 DOSAGE FORMS AND STRENGTHS

- Oral suspension — 40% (w/v) in a 240 mL multiple-dose HDPE plastic bottle or 70 mL multiple dose glass vial for oral administration (3)

4 CONTRAINDICATIONS

- Known or suspected perforation of the GI tract (4)
- Known obstruction of the GI tract (4)
- Conditions associated with high risk of GI perforation (4)
- Patients with tracheo-esophageal fistula (4)
- Known severe hypersensitivity to barium sulfate or any of the excipients of VARIBAR NECTAR (4)

5 WARNINGS AND PRECAUTIONS

- Hypersensitivity reactions: Emergency equipment and trained personnel should be immediately available (5.1)
- Intra-abdominal barium leakage: May occur in conditions such as GI fistula, ulcer, inflammatory bowel disease, appendicitis or diverticulitis, severe stenosis or obstructing lesions of the GI tract (5.2)
- Delayed GI transit and obstruction: Patients should maintain adequate hydration in days following a barium sulfate procedure to avoid obstruction or impaction (5.3)
- Aspiration pneumonitis: Aspiration may occur during the modified barium swallow examination. Monitor the patient for aspiration (5.4)

6 ADVERSE REACTIONS

Common adverse reactions include nausea, vomiting, diarrhea and abdominal cramping (6)

To report SUSPECTED ADVERSE REACTIONS, contact Bracco Diagnostics Inc at 1-800-257-5181 or FDA at 1-800-FDA-1088 or www.fda.gov/medwatch

FULL PRESCRIBING INFORMATION

1 INDICATIONS AND USAGE

VARIBAR NECTAR is indicated for use in modified barium swallow examinations to evaluate the oral and pharyngeal function and morphology in adult and pediatric patients.

2 DOSAGE AND ADMINISTRATION

2.1 Recommended Dosing

- The recommended dose of VARIBAR NECTAR administered orally by syringe, spoon, or cup:
  - Adults                                                                                    5 mL
  - Pediatric patients 6 months and older                         1-3 mL
  - Pediatric patients younger than 6 months of age    0.5-1 mL
    (This amount may be administered by an oral syringe or, alternatively, an infant bottle)
- During a single modified barium swallow examination, multiple doses of VARIBAR NECTAR may be administered as appropriate to assess the patient during multiple swallows and different radiographic views.
- The maximum cumulative dose is 30 mL.
- Once opened, write the discard after date on the immediate container label. Discard any unused product after 21 days.

2.2 Important Administration Instructions

For oral use only.

Encourage patients to hydrate following the barium sulfate procedure.

3 DOSAGE FORMS AND STRENGTHS

Oral suspension: barium sulfate (40% w/v) supplied in both a multiple dose HDPE plastic bottle and a multiple-dose glass vial as a suspension for oral administration. Each bottle contains 240 mL of suspension; each glass vial contains 70 mL of suspension.

4 CONTRAINDICATIONS

VARIBAR NECTAR is contraindicated in patients with:

- known or suspected perforation of the GI tract
- known obstruction of the GI tract
- high risk of GI perforation such as those with a recent prior GI perforation, acute GI hemorrhage or ischemia, toxic megacolon, severe ileus, post GI surgery or biopsy, acute GI injury or burn, or recent radiotherapy to the pelvis
- high risk for aspiration such as those with known or suspected tracheo-esophageal fistula or obtundation
- known severe hypersensitivity to barium sulfate or any of the excipients of VARIBAR NECTAR

5 WARNINGS AND PRECAUTIONS

5.1 Hypersensitivity Reactions

Barium sulfate preparations contain a number of excipients, including natural and artificial flavors and may induce serious hypersensitivity reactions. The manifestations include hypotension, bronchospasm and other respiratory impairments, dermal reactions including rashes, urticaria and itching. A history of bronchial asthma, atopy or a previous reaction to a contrast agent may increase the risk for hypersensitivity reactions. Emergency equipment and trained personnel should be immediately available for treatment of a hypersensitivity reaction.

5.2 Intra-abdominal Barium Leakage

The use of VARIBAR NECTAR is contraindicated in patients at high risk of perforation of the GI tract [see Contraindications (4)]. Administration of VARIBAR NECTAR may result in leakage of barium at any level of the GI tract in the presence of conditions such as carcinomas, GI fistula, inflammatory bowel disease, gastric or duodenal ulcer, appendicitis or diverticulitis, and in patients with a severe stenosis at any level of the GI tract, especially if it is distal to the stomach. The barium leakage has been associated with peritonitis and granuloma formation.

5.3 Delayed Gastrointestinal Transit and Obstruction

Orally administered barium sulfate may accumulate proximal to a constricting lesion of the colon, causing obstruction or impaction with development of baroliths (inspissated barium associated with feces) and may lead to abdominal pain, appendicitis, bowel obstruction, or rarely perforation. Patients with the following conditions are at higher risk for developing obstruction or baroliths: severe stenosis at any level of the GI tract, impaired GI motility, electrolyte imbalance, dehydration, on a low residue diet, taking medications that delay GI motility, constipation, pediatric patients with cystic fibrosis or Hirschsprung disease, and the elderly [see Use in Specific Populations (8.4, 8.5)]. To reduce the risk of delayed GI transit and obstruction, patients should maintain adequate hydration following a barium sulfate procedure.

5.4 Aspiration Pneumonitis

The use of VARIBAR NECTAR is contraindicated in patients with tracheo-esophageal fistula [see Contraindications (4)]. Oral administration of barium is associated with aspiration pneumonitis, especially in patients with a history of food aspiration or with compromised swallowing mechanism. Vomiting following oral administration of barium sulfate may lead to aspiration pneumonitis.

In patients at risk for aspiration, begin the procedure with a small ingested volume of VARIBAR NECTAR. Aspiration of small volumes of barium sulfate may occur during the modified barium swallow procedure in some patients. Monitor the patient closely for aspiration, discontinue administration if aspiration is suspected and monitor for development of aspiration pneumonitis.

5.5 Systemic Embolization

Barium sulfate products may occasionally intravasate into the venous drainage of the large bowel and enter the circulation as a "barium embolus" leading to potentially fatal complications which include systemic and pulmonary embolism, disseminated intravascular coagulation, septicemia and prolonged severe hypotension. Although this complication is exceedingly uncommon after oral administration of barium sulfate products, monitor patients for potential intravasation when administering barium sulfate.

6 ADVERSE REACTIONS

The following adverse reactions have been identified from spontaneous reporting or clinical studies of barium sulfate administered orally. Because the reactions are reported voluntarily from a population of uncertain size, it is not always possible to reliably estimate their frequency or to establish a causal relationship to drug exposure:

- Nausea, vomiting, diarrhea and abdominal cramping
- Serious adverse reactions and fatalities include aspiration pneumonitis, barium sulfate impaction, intestinal perforation with consequent peritonitis and granuloma formation, vasovagal and syncopal episodes

8 USE IN SPECIFIC POPULATIONS

8.1 Pregnancy

Risk Summary

VARIBAR NECTAR is not absorbed systemically following oral administration, and maternal use is not expected to result in fetal exposure to the drug [see Clinical Pharmacology (12.3)].

8.2 Lactation

Risk Summary

VARIBAR NECTAR is not absorbed systemically by the mother following oral administration, and breastfeeding is not expected to result in exposure of the infant to VARIBAR NECTAR [see Clinical Pharmacology (12.3)].

8.4 Pediatric Use

The efficacy of VARIBAR NECTAR in pediatric patients from birth to less than 17 years of age is based on successful opacification of the oropharynx during modified barium swallow examinations [see Clinical Pharmacology (12.1)]. Safety and dosing recommendations in pediatric patients are based on clinical experience [see Dosage and Administration (2.1)].

VARIBAR NECTAR is contraindicated in pediatric patients with tracheo-esophageal fistula [see Contraindications (4)]. Pediatric patients with a history of asthma or food allergies may be at increased risk for development of hypersensitivity reactions [see Warnings and Precautions (5.1)]. Patients with cystic fibrosis or Hirschsprung disease should be monitored for small bowel obstruction after use [see Warnings and Precautions (5.3)]

8.5 Geriatric Use

Clinical studies of VARIBAR NECTAR do not include sufficient numbers of subjects aged 65 and over to determine whether they respond differently from younger subjects. Other reported clinical experience has not identified differences in responses between the elderly and younger patients. In general, dose selection for an elderly patient should be cautious, usually starting at the low end of the dosing range, reflecting the greater frequency of decreased hepatic, renal, or cardiac function, and of concomitant disease or other drug therapy.

11 DESCRIPTION

VARIBAR NECTAR (barium sulfate) is a radiographic contrast agent for oral administration that is supplied as a 40% w/v, smooth, off- white to lightly colored free-flowing suspension with an apple aroma. The active ingredient is designated chemically as BaSO4 which has a density of 4.5 g/cm^3, a molecular weight of 233.4 g/mol, and the following chemical structure:

VARIBAR NECTAR has a viscosity of 300 cPs and contains the following excipients: carboxymethylcellulose sodium, citric acid, glycerin, maltodextrin, natural and artificial apple flavor, polysorbate 80, potassium sorbate, purified water, saccharin sodium, simethicone emulsion, sodium benzoate, sodium citrate, xanthan gum, and xylitol.

12 CLINICAL PHARMACOLOGY

12.1 Mechanism of Action

Due to its high atomic number, barium (the active ingredient in VARIBAR NECTAR) is opaque to x-rays and therefore acts as a positive contrast agent for radiographic studies.

12.2 Pharmacodynamics

Barium sulfate is biologically inert and has no known pharmacological effects.

12.3 Pharmacokinetics

Under physiological conditions, barium sulfate passes through the gastrointestinal tract in an unchanged form and is absorbed only in pharmacologically insignificant amounts.

13 NONCLINICAL TOXICOLOGY

13.1 Carcinogenesis, Mutagenesis, Impairment of Fertility

No animal studies have been performed to evaluate the carcinogenic potential of barium sulfate or potential effects on fertility.

16 HOW SUPPLIED/STORAGE AND HANDLING

How Supplied

VARIBAR NECTAR is supplied in both a multiple-dose HDPE bottle containing 240 mL of barium sulfate (40% w/v) and a multiple-dose glass vial containing 70 mL of barium sulfate (40% w/v).

Provided as: 12 x 240 mL bottles (NDC 32909-116-00); 12 x 70 mL vials (32909-116-55).

Storage and Handling

Store at USP controlled room temperature 20°C to 25°C (68° F to 77° F). Protect from freezing.

Once opened, VARIBAR NECTAR may be used for up to 21 days when stored at USP controlled room temperature, 20°C to 25°C (68° F to 77° F).

17 PATIENT COUNSELING INFORMATION

After administration, advise patients to:

- Maintain adequate hydration [see Dosage and Administration (2.2) and Warnings and Precautions (5.3)].
- Seek medical attention for worsening of constipation or slow gastrointestinal passage [see Warnings and Precautions (5.3)].
- Seek medical attention for any delayed onset of hypersensitivity: rash, urticaria, or respiratory difficulty [see Warnings and Precautions (5.1)].

Rx only

Manufactured for
Bracco Diagnostics Inc.
Monroe Township, NJ 08831
by EZEM Canada Inc
Anjou (Quebec) Canada H1J 2Z4

Revised August 2024

CL10FD-02

PACKAGE LABEL

Varibar® Nectar - Barium Sulfate Oral Suspension
NDC: 32909-116-00

240 mL Varibar® Nectar Internal Label

NDC: 32909-116-55

70 mL Varibar® Nectar Internal Label